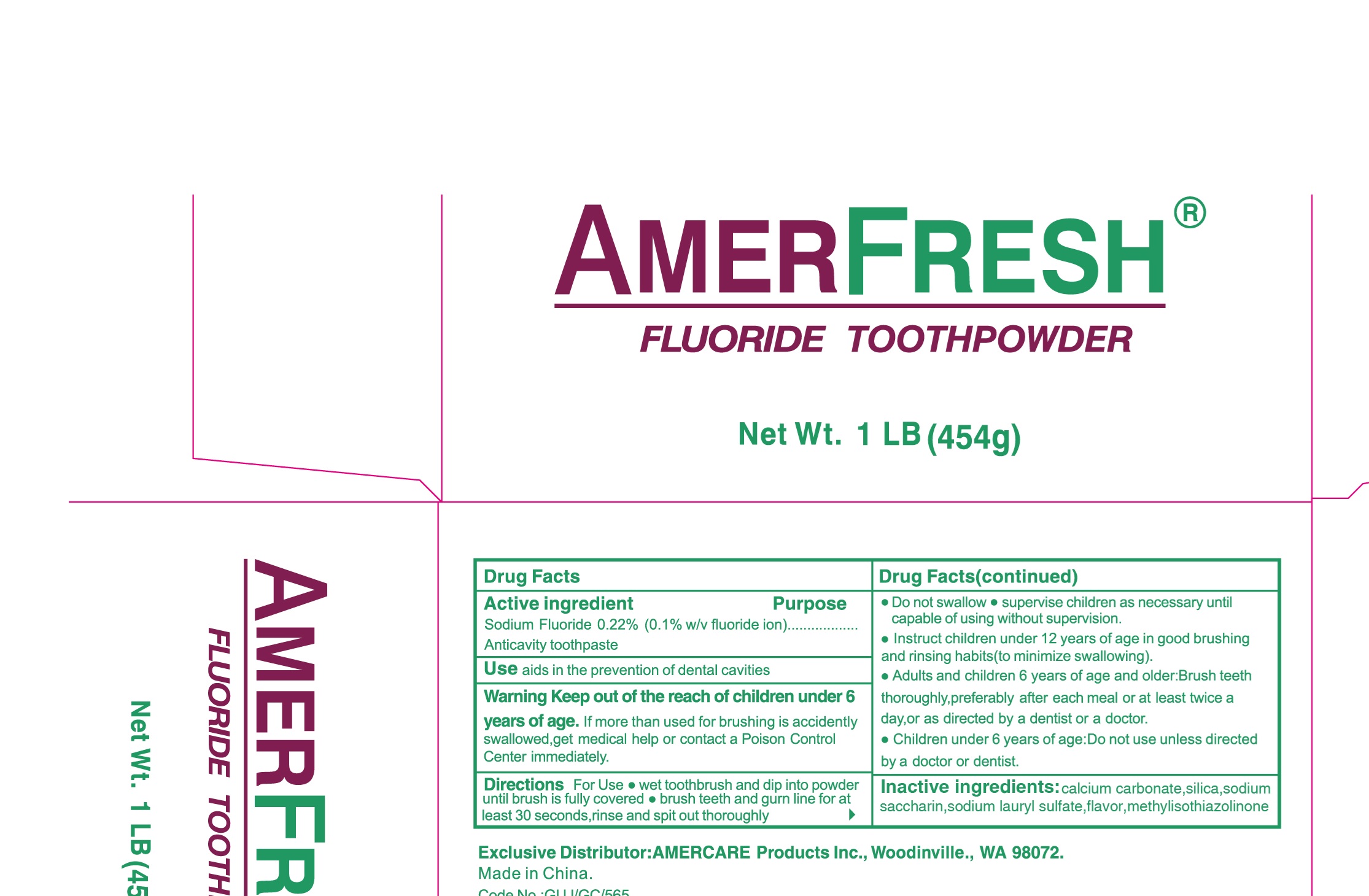 DRUG LABEL: Amerfresh Toothpowder
NDC: 85162-007 | Form: POWDER
Manufacturer: Yangzhou ONE & ONLY Personal Care Products Co., LTD
Category: otc | Type: HUMAN OTC DRUG LABEL
Date: 20250813

ACTIVE INGREDIENTS: SODIUM FLUORIDE 0.1 g/100 g
INACTIVE INGREDIENTS: CALCIUM CARBONATE; METHYLISOTHIAZOLINONE; HYDRATED SILICA; SODIUM LAURYL SULFATE; POTASSIUM SODIUM SACCHARATE

85162-007, Amerfresh Fluoride Toothpowder

Active ingredients

Sodium Fluoride 0.22%(0.1 w/v Fluoride ion)

Purpose

Anticavity toothpaste

Uses

aids in the prevention of dental cavities.

Warnings

Keep out of the reach of children under 6 years of age. If more than used for brushing is accidently swallowed,get medical help or contact a Poison Control Center immediately.

Keep out of reach of children under 6 years of age.

Directions

For Use:

- Wet toothbrush and dip into powder until brush is fully covered.
- Brush teeth and gum line for tleast 30 seconds, rinse and spit out thoroughly
- do not swallow .
- supervise children as necessary until capable of useing without supervision
- instruct children under 12 years of age in good brushing and rinsing habits (to minimize swallowing).
- Adults and children 6 years of age and older:Brush teeth thoroughly,preferably after each meal or at least twice a day,or as directed by a dentist or a physician.
- Children under 6 years of age:do not use unless directed by a doctor or dentist.

INACTIVE INGREDIENT

calcium carbonate, silica,sodium lauryl sulfate, flavor, sodium sacharine, methylisothiazolinone